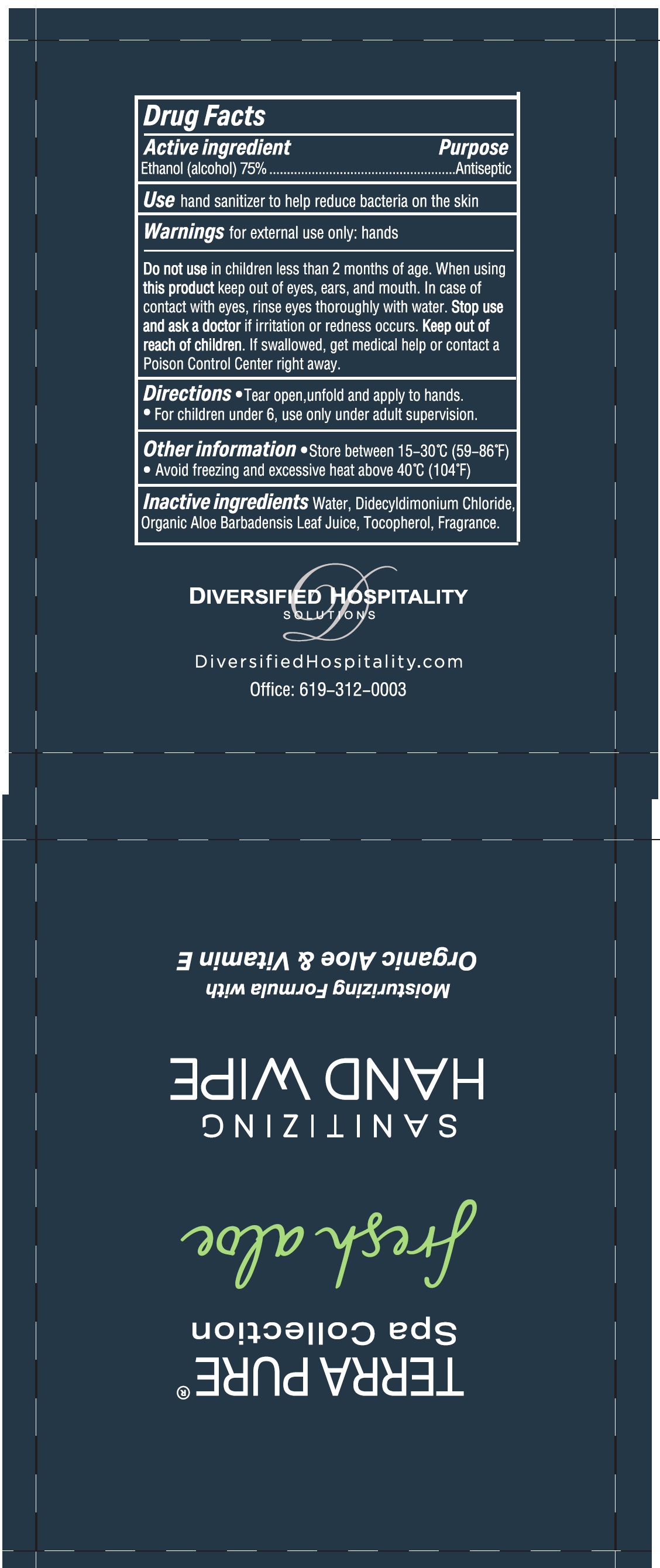 DRUG LABEL: Terra Pure Sanitizing Hand wipe
NDC: 77849-011 | Form: CLOTH
Manufacturer: Yangzhou Eco-Amenities CO., Ltd
Category: otc | Type: HUMAN OTC DRUG LABEL
Date: 20210119

ACTIVE INGREDIENTS: ALCOHOL 75 mL/100 mL
INACTIVE INGREDIENTS: WATER; DIDECYLDIMONIUM CHLORIDE; ALOE VERA LEAF; TOCOPHEROL

Terra Pure Sanitizing Hand wipe

Active ingredient

Ethanol (alcohol) 75%

Purpose

Antiseptic

Use

hand sanitizer to help reduce bacteria on the skin

Warnings

for external use only: hands

Do not use

in children less than 2 months of age.

When using this product

keep out of eyes, ears, and mouth. In case of contact with eyes, rinse eyes thoroughly with water.

Stop use and ask a doctor

if irritation and redness occurs.

Keep out of reach of children.

If swallowed, get medical help or contact a Poison Control Center right away.

Directions

- Tear open, unfold and apply to hands.
- For children under 6, use only under adult supervision.

Other information

- Store between 15-30°C (59-86°F)
- Avoid freezing and excessive heat above 40°C (104°F)

Inactive ingredients

Water, Didecyldimonium Chloride, Organic Aloe Barbadensis Leaf Juice, Tocopherol, Fragrance.